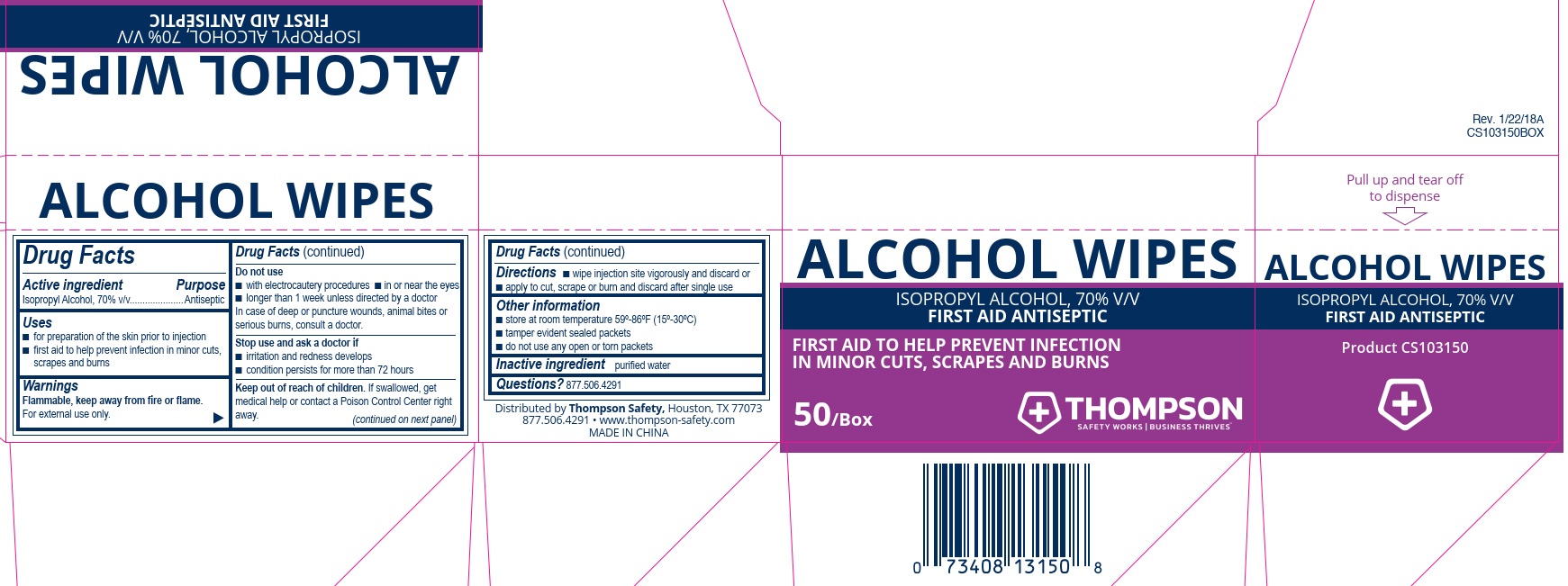 DRUG LABEL: Thompson Alcohol
NDC: 73408-033 | Form: SWAB
Manufacturer: Thompson
Category: otc | Type: HUMAN OTC DRUG LABEL
Date: 20260108

ACTIVE INGREDIENTS: ISOPROPYL ALCOHOL 0.7 mL/1 mL
INACTIVE INGREDIENTS: WATER

Thompson Alcohol Wipes

Drug Facts

Active ingredient

Isopropyl Alcohol, 70% v/v

Purpose

Antiseptic

Uses

- for preperation of the skin prior to injection
- first aid to help prevent infection in minor cuts, scrapes and burns

Warnings

Flammable, keep away from fire or flame.

For external use only.

Do not use

- with electrocautery procedures
- in or near the eyes
- longer than 1 week unless directed by a doctor

In case of deep or puncture wounds, animal bites or serious burns, consult a doctor.

Stop use and ask a doctor if

- irritation and redness develops
- condition persists for more than 72 hours

Keep out of reach of children. If swallowed, get medical help or contact a Poison Control Center right away.

Directions

- wipe injection site vigorously and discard or
- apply to cut, scrape or burn and discard after single use

Other information

- store at room temperature 59º-86ºF (15º-30ºC)
- tamper evident sealed apckets
- do not use any open or torn packets

Inactive ingredient purified water

Questions? 877.506.4291

PACKAGE LABEL

Alcohol Wipes

Isppropyl Alcohol, 70% V/V

First Aid Antiseptic

First aid to help prevent infection in minor cuts, scrapes and burns

50/Box

Thompson

Safety Works | Business Thrives™